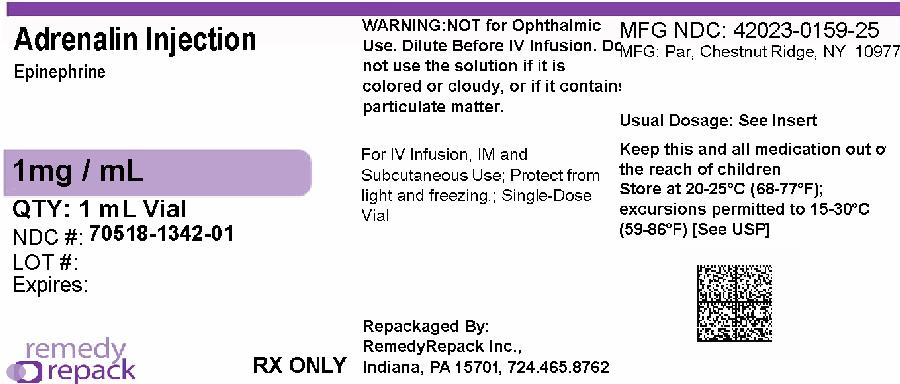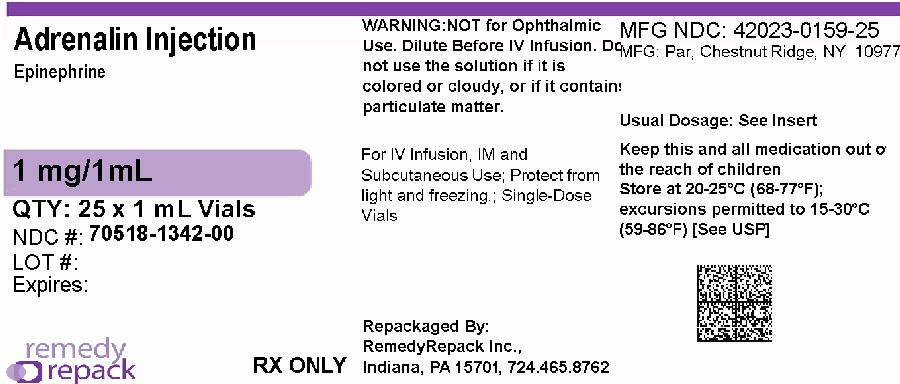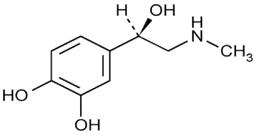 DRUG LABEL: Adrenalin
NDC: 70518-1342 | Form: INJECTION
Manufacturer: REMEDYREPACK INC.
Category: prescription | Type: HUMAN PRESCRIPTION DRUG LABEL
Date: 20260121

ACTIVE INGREDIENTS: EPINEPHRINE 1 mg/1 mL
INACTIVE INGREDIENTS: SODIUM CHLORIDE 7.3 mg/1 mL; SODIUM METABISULFITE 0.457 mg/1 mL; SODIUM HYDROXIDE 1 mg/1 mL; TARTARIC ACID 2.25 mg/1 mL; EDETATE DISODIUM 0.2 mg/1 mL; HYDROCHLORIC ACID; WATER

HIGHLIGHTS OF PRESCRIBING INFORMATION

These highlights do not include all the information needed to use ADRENALIN safely and effectively. See full prescribing information for ADRENALIN.
ADRENALIN (epinephrine injection) 1 mg/mL, for
intramuscular, subcutaneous, and intravenous use
Initial U.S. Approval: 1939

RECENT MAJOR CHANGES

Indications and Usage (1.2) 01/2019

Dosage and Administration (2.3) 01/2019

Warnings and Precautions (5.3, 5.4, 5.5, 5.6, 5.7) 01/2019

1 INDICATIONS AND USAGE

Adrenalin®is a non-selective alpha and beta adrenergic agonist indicated for:

- Emergency treatment of allergic reactions (Type 1), including anaphylaxis (1.1)
- To increase mean arterial blood pressure in adult patients with hypotension associated with septic shock (1.2)

2 DOSAGE AND ADMINISTRATION

- Anaphylaxis:
  - Adults and Children 30 kg (66 lbs) or more: 0.3 mg to 0.5 mg (0.3 mL to 0.5 mL) intramuscularly or subcutaneously into anterolateral aspect of the thigh every 5 to 10 minutes as necessary (2.2)
  - Children 30 kg (66 lbs) or less: 0.01 mg/kg (0.01 mL/kg), up to 0.3 mg (0.3 mL), intramuscularly or subcutaneously into anterolateral aspect of the thigh every 5 to 10 minutes as necessary (2.2)
- Hypotension associated with septic shock:
  - Dilute epinephrine in dextrose solution prior to infusion (2.3)
  - Infuse epinephrine into a large vein (2.3)
  - Intravenous infusion rate of 0.05 mcg/kg/min to 2 mcg/kg/min, titrated to achieve desired mean arterial pressure (2.3)
  - Wean gradually (2.3)
  - See Full Prescribing Information for instructions on dilution and administration of the injection.

3 DOSAGE FORMS AND STRENGTHS

Injection: 1 mg/mL single dose vial and 30 mg/30 mL (1 mg/mL) multiple dose vial (3)

4 CONTRAINDICATIONS

None (4)

5 WARNINGS AND PRECAUTIONS

- Do not inject into buttocks, digits, hands, or feet (5.1)
- Avoid extravasation into tissues, which can cause local necrosis (5.3)
- May aggravate angina pectoris or produce ventricular arrhythmias (5.7)

6 ADVERSE REACTIONS

Common adverse reactions to systemically administered epinephrine include anxiety, tremor, weakness, dizziness, sweating, palpitations and pallor (6)

To report SUSPECTED ADVERSE REACTIONS, contact Par Pharmaceutical at 1-800-828-9393 or FDA at 1-800-FDA-1088 or www.fda.gov/medwatch.

7 DRUG INTERACTIONS

- Drugs that counter the pressor effects of epinephrine include alpha blockers, vasodilators such as nitrates, diuretics, antihypertensives and ergot alkaloids. (7.1)
- Drugs that potentiate the effects of epinephrine include sympathomimetics, beta blockers, tricyclic antidepressants, MAO inhibitors, COMT inhibitors, clonidine, doxapram, oxytocin, levothyroxine sodium, quinidine and certain antihistamines. (7.2)
- Drugs that increase the arrhythmogenic potential of epinephrine include beta blockers, cyclopropane and halogenated hydrocarbon anesthetics, antihistamines, exogenous thyroid hormones, diuretics, and cardiac glycosides. Observe for development of cardiac arrhythmias. (7.3)
- Potassium-depleting drugs, including corticosteroids, diuretics, and theophylline, potentiate the hypokalemic effects of epinephrine. (7.4)

8 USE IN SPECIFIC POPULATIONS

- Elderly patients and pregnant women may be at greater risk of developing adverse reactions when epinephrine is administered parenterally (8.1, 8.5)
- Pregnancy: May cause fetal harm (8.1)

FULL PRESCRIBING INFORMATION

1 INDICATIONS AND USAGE

1.1 Anaphylaxis

Emergency treatment of allergic reactions (Type I), including anaphylaxis, which may result from insect stings or bites, foods, drugs, sera, diagnostic testing substances and other allergens, as well as idiopathic anaphylaxis or exercise-induced anaphylaxis.

1.2 Hypotension associated with Septic Shock

Adrenalinis indicated to increase mean arterial blood pressure in adult patients with hypotension associated with septic shock.

2 DOSAGE AND ADMINISTRATION

2.1 General Considerations

Inspect visually for particulate matter and discoloration prior to administration; solution should be clear and colorless. Do not use if the solution is colored or cloudy, or if it contains particulate matter.

2.2 Anaphylaxis

Inject Adrenalin intramuscularly or subcutaneously into the anterolateral aspect of the thigh, through clothing if necessary. When administering to a child, to minimize the risk of injection related injury, hold the leg firmly in place and limit movement prior to and during an injection. The injection may be repeated every 5 to 10 minutes as necessary. For intramuscular administration, use a needle long enough (at least 1/2 inch) to ensure the injection is administered into the muscle. Monitor the patient clinically for the severity of the allergic reaction and potential cardiac effects of the drug, and repeat as needed. Do not administer repeated injections at the same site, as the resulting vasoconstriction may cause tissue necrosis.

Adults and Children 30 kg (66 lbs) or more: 0.3 to 0.5 mg (0.3 to 0.5 mL) of undiluted Adrenalin administered intramuscularly or subcutaneously in the anterolateral aspect of the thigh, up to a maximum of 0.5 mg (0.5 mL) per injection, repeated every 5 to 10 minutes as necessary. Monitor clinically for reaction severity and cardiac effects.

Children less than 30 kg (66 lbs): 0.01 mg/kg (0.01 mL/kg) of undiluted Adrenalin administered intramuscularly or subcutaneously in the anterolateral aspect of the thigh, up to a maximum of 0.3 mg (0.3 mL) per injection, repeated every 5 to 10 minutes as necessary. Monitor clinically for reaction severity and cardiac effects.

2.3 Hypotension associated with Septic Shock

Dilute 1 mL (1 mg) of epinephrine from its vial to 1,000 mL of a 5 percent dextrose or 5 percent dextrose and sodium chloride solution to produce a 1 mcg per mL dilution. Administration in saline solution alone is not recommended. If indicated, administer whole blood or plasma separately.

Whenever possible, give infusions of epinephrine into a large vein. Avoid using a catheter tie-in technique, because the obstruction to blood flow around the tubing may cause stasis and increased local concentration of the drug. Avoid the veins of the leg in elderly patients or in those suffering from occlusive vascular diseases.

To provide hemodynamic support in septic shock associated hypotension in adult patients, the suggested dosing infusion rate of intravenously administered epinephrine is 0.05 to 2 mcg/kg/min, and is titrated to achieve a desired mean arterial pressure (MAP). The dosage may be adjusted periodically, such as every 10 to 15 minutes, in increments of 0.05 to 0.2 mcg/kg/min, to achieve the desired blood pressure goal.

After hemodynamic stabilization, wean incrementally over time, such as by decreasing doses of epinephrine every 10 minutes to determine if the patient can tolerate gradual withdrawal.

Adrenalin diluted in 5 percent dextrose solutions or 5 percent dextrose and sodium chloride solutions are stable for 4 hours at room temperature or 24 hours under refrigerated conditions.

3 DOSAGE FORMS AND STRENGTHS

Adrenalin injection: clear, colorless solution supplied as 1 mg/1 mL in a single dose clear glass vial and as 30 mg/30 mL (1 mg/mL) in a multiple dose amber glass vial.

4 CONTRAINDICATIONS

None.

5 WARNINGS AND PRECAUTIONS

5.1 Incorrect Locations of Injection for Anaphylaxis

Injection into the anterolateral aspect of the thigh (vastus lateralis muscle) is the most appropriate location for administration because of its location, size, and available blood flow. Injection into (or near) smaller muscles, such as in the deltoid, is not recommended.

Do not administer repeated injections of epinephrine at the same site, as the resulting vasoconstriction may cause tissue necrosis.

Do not inject into buttock. Injection into the buttock may not provide effective treatment of anaphylaxis and has been associated with the development of Clostridial infections (gas gangrene).

Do not inject into digits, hands, or feet. Epinephrine is a strong vasoconstrictor. Accidental injection into the digits, hands or feet may result in loss of blood flow to the affected area and tissue necrosis.

5.2 Serious Infections at the Injection Site

Rare cases of serious skin and soft tissue infections, including necrotizing fasciitis and myonecrosis caused by Clostridia (gas gangrene), have been reported at the injection site following epinephrine injection for anaphylaxis. Advise patients to seek medical care if they develop signs or symptoms of infection, such as persistent redness, warmth, swelling, or tenderness, at the epinephrine injection site.

5.3 Extravasation and Tissue Necrosis with Intravenous Infusion

Avoid extravasation of epinephrine into the tissues, to prevent local necrosis. When Adrenalin is administered intravenously, check the infusion site frequently for free flow. Blanching along the course of the infused vein, sometimes without obvious extravasation, may be attributed to vasa vasorum constriction with increased permeability of the vein wall, permitting some leakage. This also may progress on rare occasions to superficial slough. Hence, if blanching occurs, consider changing the infusion site at intervals to allow the effects of local vasoconstriction to subside.

There is potential for gangrene in a lower extremity when infusions of catecholamine are given in an ankle vein.

Antidote for Extravasation Ischemia:To prevent sloughing and necrosis in areas in which extravasation has taken place, infiltrate the area with 10 mL to 15 mL of saline solution containing from 5 mg to 10 mg of phentolamine, an adrenergic blocking agent. Use a syringe with a fine hypodermic needle, with the solution being infiltrated liberally throughout the area, which is easily identified by its cold, hard, and pallid appearance. Sympathetic blockade with phentolamine causes immediate and conspicuous local hyperemic changes if the area is infiltrated within 12 hours.

5.4 Hypertension

Because individual response to epinephrine may vary significantly, monitor blood pressure frequently and titrate to avoid excessive increases in blood pressure.

Patients receiving monoamine oxidase inhibitors (MAOI) or antidepressants of the triptyline or imipramine types may experience severe, prolonged hypertension when given epinephrine.

5.5 Pulmonary Edema

Epinephrine increases cardiac output and causes peripheral vasoconstriction, which may result in pulmonary edema.

5.6 Renal Impairment

Epinephrine constricts renal blood vessels, which may result in oliguria or renal impairment.

5.7 Cardiac Arrhythmias and Ischemia

Epinephrine may induce cardiac arrhythmias and myocardial ischemia in patients, especially patients suffering from coronary artery disease, or cardiomyopathy.

5.8 Allergic Reactions Associated with Sulfite

Adrenalin contains sodium bisulfite which may cause mild to severe allergic reactions including anaphylaxis or asthmatic episodes in susceptible individuals. However, the presence of bisulfite in this product should not preclude its use for the treatment of serious allergic or other emergency situations even if the patient is sulfite-sensitive, as the alternatives to using epinephrine in a life-threatening situation may not be satisfactory.

6 ADVERSE REACTIONS

Common adverse reactions to systemically administered epinephrine include anxiety, apprehensiveness, restlessness, tremor, weakness, dizziness, sweating, palpitations, pallor, nausea and vomiting, headache, and respiratory difficulties. These symptoms occur in some persons receiving therapeutic doses of epinephrine, but are more likely to occur in patients with heart disease, hypertension, or hyperthyroidism [ see Warnings and Precautions (5.7)] .

The true incidence of adverse reactions associated with the systemic use of epinephrine is difficult to determine. Adverse reactions reported in observational trials, case reports, and studies are listed below by body system:

Cardiovascular: angina, arrhythmias, hypertension, pallor, palpitations, tachyarrhythmia, tachycardia, vasoconstriction, ventricular ectopy and stress cardiomyopathy.

Rapid rises in blood pressure associated with epinephrine use have produced cerebral hemorrhage, particularly in elderly patients with cardiovascular disease [ see Warnings and Precautions (5.7)] .

Neurological: disorientation, impaired memory, panic, psychomotor agitation, sleepiness, tingling.

Psychiatric: anxiety, apprehensiveness, restlessness.

Other:

Patients with Parkinson’s disease may experience psychomotor agitation or a temporary worsening of symptoms [ see Warnings and Precautions (5.7)] .

Diabetic patients may experience transient increases in blood sugar.

Injection into the buttock has resulted in cases of gas gangrene [ see Warnings and Precautions (5.1)] .

Rare cases of serious skin and soft tissue infections, including necrotizing fasciitis and myonecrosis caused by Clostridia (gas gangrene), have been reported following epinephrine injection in the thigh [ see Warnings and Precautions (5.2)].

7 DRUG INTERACTIONS

7.1 Drugs Antagonizing Pressor Effects of Epinephrine

- α-blockers, such as phentolamine
- Vasodilators, such as nitrates
- Diuretics
- Antihypertensives
- Ergot alkaloids
- Phenothiazine antipsychotics

7.2 Drugs Potentiating Pressor Effects of Epinephrine

- Sympathomimetics
- β-blockers, such as propranolol
- Tricyclic anti-depressants
- Monoamine oxidase (MAO) inhibitors
- Catechol-O-methyl transferase (COMT) inhibitors, such as entacapone
- Clonidine
- Doxapram
- Oxytocin

7.3 Drugs Potentiating Arrhythmogenic Effects of Epinephrine

Cardiac arrhythmias are more common among patients receiving any of the following drugs [ see Warnings and Precautions (5.7)and Adverse Reactions (6)] .

- β-blockers, such as propranolol
- Cyclopropane or halogenated hydrocarbon anesthetics, such as halothane
- Antihistamines
- Thyroid hormones
- Diuretics
- Cardiac glycosides, such as digitalis glycosides
- Quinidine

7.4 Drugs Potentiating Hypokalemic Effects of Epinephrine

- Potassium depleting diuretics
- Corticosteroids
- Theophylline

8 USE IN SPECIFIC POPULATIONS

8.1 Pregnancy

Risk Summary

Prolonged experience with epinephrine use in pregnant women over several decades, based on published literature, do not identify a drug associated risk of major birth defects, miscarriage or adverse maternal or fetal outcomes. However, there are risks to the mother and fetus associated with epinephrine use during labor or delivery (see Clinical Considerations). In animal reproduction studies, epinephrine administered by the subcutaneous route to pregnant rabbits, mice, and hamsters, during the period of organogenesis, resulted in adverse developmental effects (including gastroschisis, and embryonic lethality, and delayed skeletal ossification) at doses approximately 2 times the maximum recommended daily intramuscular, subcutaneous, or intravenous dose (see Data).

The estimated background risk of major birth defects and miscarriage for the indicated population is unknown. All pregnancies have a background risk of birth defect, loss, or other adverse outcomes. In the United States general population, the estimated background risk of major birth defects and miscarriage in clinically recognized pregnancies is 2 to 4% and 15 to 20%, respectively.

Clinical Considerations

Disease-associated maternal and/or embryo/fetal risk

During pregnancy, anaphylaxis can be catastrophic and can lead to hypoxic-ischemic encephalopathy and permanent central nervous system damage or death in the mother and, more commonly, in the fetus or neonate. The prevalence of anaphylaxis occurring during pregnancy is reported to be approximately 3 cases per 100,000 deliveries.

Management of anaphylaxis during pregnancy is similar to management in the general population. Epinephrine is the first line-medication of choice for treatment of anaphylaxis; it should be used in the same manner in pregnant and non-pregnant patients. In conjunction with the administration of epinephrine, the patient should seek immediate medical or hospital care.

Hypotension associated with septic shock is a medical emergency in pregnancy which can be fatal if left untreated. Delaying treatment in pregnant women with hypotension associated with septic shock may increase the risk of maternal and fetal morbidity and mortality. Life-sustaining therapy for the pregnant woman should not be withheld due to potential concerns regarding the effects of epinephrine on the fetus.

Labor or Delivery

Epinephrine usually inhibits spontaneous or oxytocin induced contractions of the pregnant human uterus and may delay the second stage of labor. Avoid epinephrine during the second stage of labor. In dosage sufficient to reduce uterine contractions, the drug may cause a prolonged period of uterine atony with hemorrhage. Avoid epinephrine in obstetrics when maternal blood pressure exceeds 130/80 mmHg.

Although epinephrine may improve maternal hypotension associated with septic shock and anaphylaxis, it may result in uterine vasoconstriction, decreased uterine blood flow, and fetal anoxia.

Data

Animal Data

In an embryofetal development study with pregnant rabbits dosed during the period of organogenesis (on days 3 to 5, 6 to 7 or 7 to 9 of gestation), epinephrine caused teratogenic effects (including gastroschisis) at doses approximately 15 times the maximum recommended intramuscular, subcutaneous, or intravenous dose (on a mg/m^2basis at a maternal subcutaneous dose of 1.2 mg/kg/day for two to three days). Animals treated on days 6 to 7 had decreased number of implantations.

In an embryofetal development study, pregnant mice were administered epinephrine (0.1 to 10 mg/kg/day) on Gestation Days 6 to 15. Teratogenic effects, embryonic lethality, and delays in skeletal ossification were observed at approximately 3 times the maximum recommended intramuscular, subcutaneous, or intravenous dose (on a mg/m^2basis at maternal subcutaneous dose of 1 mg/kg/day for 10 days). These effects were not seen in mice at approximately 2 times the maximum recommended daily intramuscular or subcutaneous dose (on a mg/m^2basis at a subcutaneous maternal dose of 0.5 mg/kg/day for 10 days).

In an embryofetal development study with pregnant hamsters dosed during the period of organogenesis from gestation days 7 to 10, epinephrine produced reductions in litter size and delayed skeletal ossification at doses approximately 2 times the maximum recommended intramuscular, subcutaneous, or intravenous dose (on a mg/m^2basis at a maternal subcutaneous dose of 0.5 mg/kg/day).

8.2 Lactation

Risk Summary

There is no information regarding the presence of epinephrine in human milk or the effects of epinephrine on the breastfed infant or on milk production. However, due to its poor oral bioavailability and short half-life, epinephrine exposure is expected to be very low in the breastfed infant.

Epinephrine is the first-line medication of choice for treatment of anaphylaxis; it should be used in the same manner for anaphylaxis in breastfeeding and non-breastfeeding patients.

8.4 Pediatric Use

Clinical use data support weight-based dosing for treatment of anaphylaxis in pediatric patients, and other reported clinical experience with the use of epinephrine suggests that the adverse reactions seen in children are similar in nature and extent to those both expected and reported in adults.

Safety and effectiveness of epinephrine in pediatric patients with septic shock have not been established.

8.5 Geriatric Use

Clinical studies for the treatment of anaphylaxis have not been performed in subjects aged 65 and over to determine whether they respond differently from younger subjects. However, other reported clinical experience with use of epinephrine for the treatment of anaphylaxis has identified that geriatric patients may be particularly sensitive to the effects of epinephrine. Therefore, for the treatment of anaphylaxis, consider starting with a lower dose to take into account potential concomitant disease or other drug therapy.

Clinical studies of epinephrine for the treatment of hypotension associated with septic shock did not include sufficient numbers of subjects aged 65 and over to determine whether they respond differently from younger subjects. Other reported clinical experience has not identified differences in responses between the elderly and younger patients. In general, dose selection for an elderly patient should be cautious, usually starting at the low end of the dosing range, reflecting the greater frequency of decreased hepatic, renal, or cardiac function, and of concomitant disease or other drug therapy.

10 OVERDOSAGE

Overdosage of epinephrine may produce extremely elevated arterial pressure, which may result in cerebrovascular hemorrhage, particularly in elderly patients. Overdosage may also result in pulmonary edema because of peripheral vascular constriction together with cardiac stimulation. Epinephrine overdosage can also cause transient bradycardia followed by tachycardia and these may be accompanied by potentially fatal cardiac arrhythmias. Premature ventricular contractions may appear within one minute after injection and may be followed by multifocal ventricular tachycardia (prefibrillation rhythm). Subsidence of the ventricular effects may be followed by atrial tachycardia and occasionally by atrioventricular block. Myocardial ischemia and infarction, cardiomyopathy, extreme pallor and coldness of the skin, metabolic acidosis due to elevated blood lactic acid levels, and renal insufficiency have also been reported.

Epinephrine is rapidly inactivated in the body and treatment following overdose with epinephrine is primarily supportive. Treatment of pulmonary edema consists of a rapidly acting alpha-adrenergic blocking drug (such as phentolamine mesylate) and respiratory support. Treatment of arrhythmias consists of administration of a beta-adrenergic blocking drug (such as propranolol). If necessary, pressor effects may be counteracted by rapidly acting vasodilators or α-adrenergic blocking drugs. If prolonged hypotension follows such measures, it may be necessary to administer another pressor drug.

11 DESCRIPTION

Adrenalin (epinephrine injection, USP) is a clear, colorless, sterile solution containing 1 mg/mL epinephrine, packaged as 1 mL of solution in a single dose clear glass vial or 30 mL of solution in a multiple dose amber glass vial. In the 1 mL vial, each 1 mL of Adrenalin solution contains 1 mg epinephrine, 7.3 mg sodium chloride, 0.457 mg sodium metabisulfite, 1 mg sodium hydroxide, 2.25 mg tartaric acid, 0.20 mg disodium edetate dihydrate, 5.32 mg of 4% hydrochloric acid to adjust pH, and water for injection. In the 30 mL vial, each 1 mL of Adrenalin solution contains 1 mg epinephrine, 6.15 mg sodium chloride, 0.457 mg sodium metabisulfite, 0.920 mg sodium hydroxide, 2.25 mg tartaric acid, 0.20 mg disodium edetate dihydrate, 5.18 mg of 4% hydrochloric acid to adjust pH, 5.25 mg chlorobutanol as a preservative and water for injection. The pH range is 2.2-5.0.

Epinephrine is a sympathomimetic catecholamine. The chemical name of epinephrine is: 1,2-Benzenediol, 4-[(1R)-1-hydroxy-2-(methylamino)ethyl]-, or (-)-3,4-Dihydroxy-α-[2-(methylamino)ethyl]benzyl alcohol.

The chemical structure of epinephrine is:

The molecular weight of epinephrine is 183.2.

Epinephrine solution deteriorates rapidly on exposure to air or light, turning pink from oxidation to adrenochrome and brown from the formation of melanin.

12 CLINICAL PHARMACOLOGY

12.1 Mechanism of Action

Epinephrine acts on both alpha and beta-adrenergic receptors. The mechanism of the rise in blood pressure is 3-fold: a direct myocardial stimulation that increases the strength of ventricular contraction (positive inotropic action), an increased heart rate (positive chronotropic action), and peripheral vasoconstriction.

12.2 Pharmacodynamics

Epinephrine increases glycogenolysis, reduces glucose up take by tissues, and inhibits insulin release in the pancreas, resulting in hyperglycemia and increased blood lactic acid.

Intramuscular and subcutaneous use for anaphylaxis

Through its action on alpha-adrenergic receptors, epinephrine lessens the vasodilation and increased vascular permeability that occurs during anaphylaxis, which can lead to loss of intravascular fluid volume and hypotension.

Through its action on beta-adrenergic receptors, epinephrine causes bronchial smooth muscle relaxation and helps alleviate bronchospasm, wheezing and dyspnea that may occur during anaphylaxis.

Epinephrine also alleviates pruritus, urticaria, and angioedema and may relieve gastrointestinal and genitourinary symptoms associated with anaphylaxis because of its relaxer effects on the smooth muscle of the stomach, intestine, uterus and urinary bladder.

Intravenous use for hypotension associated with septic shock

When administered parenterally, epinephrine has a rapid onset and short duration of action.

Following intravenous administration of epinephrine, increases in systolic blood pressure and heart rate are observed. Decreases in systemic vascular resistance and diastolic blood pressure are observed at low doses of epinephrine because of β2-mediated vasodilation, but are overtaken by α1-mediated peripheral vasoconstriction at higher doses leading to increase in diastolic blood pressure. The onset of blood pressure increase following an intravenous dose of epinephrine is < 5 minutes and the time to offset blood pressure response occurs within 15 minutes. Most vascular beds are constricted including renal, splanchnic, mucosal and skin.

Epinephrine causes mydriasis when administered parenterally.

12.3 Pharmacokinetics

Following intravenous injection, epinephrine is rapidly cleared from the plasma with an effective half-life of < 5 minutes. A pharmacokinetic steady state following continuous intravenous infusion is achieved within 10‑15 minutes. In patients with septic shock, epinephrine displays dose-proportional pharmacokinetics in the infusion dose range of 0.03 to 1.7 mcg/kg/min.

Epinephrine is extensively metabolized with only a small amount excreted unchanged.

Epinephrine is rapidly degraded to vanillylmandelic acid, an inactive metabolite, by monoamine oxidase and catechol-O-methyltransferase that are abundantly expressed in the liver, kidneys and other extraneuronal tissues. The tissues with the highest contribution to removal of circulating exogenous epinephrine are the liver (32%), kidneys (25%), skeletal muscle (20%), and mesenteric organs (12%).

Specific Populations

Elderly

In a pharmacokinetic study of 45-minute epinephrine infusions given to healthy men aged 20 to 25 years and healthy men aged 60 to 65 years, the mean plasma metabolic clearance rate of epinephrine at steady state was greater among the older men (144.8 versus 78 mL/kg/min for a 0.0143 mcg/kg/min infusion).

Body Weight

Body weight has been found to influence epinephrine pharmacokinetics. Higher body weight was associated with a higher plasma epinephrine clearance and a lower concentration plateau.

13 NONCLINICAL TOXICOLOGY

13.1 Carcinogenesis, Mutagenesis, Impairment of Fertility

Long-term studies to evaluate the carcinogenic potential of epinephrine have not been conducted.

Epinephrine and other catecholamines have been shown to have mutagenic potential in vitro. Epinephrine was positive in the Salmonellabacterial reverse mutation assay, positive in the mouse lymphoma assay, and negative in the in vivomicronucleus assay. Epinephrine is an oxidative mutagen based on the E. coliWP2 Mutoxitest bacterial reverse mutation assay. This should not prevent the use of epinephrine under the conditions noted under Indications and Usage (1).

The potential for epinephrine to impair reproductive performance has not been evaluated, but epinephrine has been shown to decrease implantation in female rabbits dosed subcutaneously with 1.2 mg/kg/day (15-fold the highest human intramuscular or subcutaneous daily dose) during gestation days 3 to 9.

16 HOW SUPPLIED/STORAGE AND HANDLING

Adrenalin 1 mg/mL Single Dose Vials:

Each carton contains 25 single dose vials containing 1 mg/mL Adrenalin (epinephrine injection, USP) solution in a 3 mL clear glass vial.

NDC: 70518-1342-00

NDC: 70518-1342-01

PACKAGING: 25 in 1 CARTON

PACKAGING: 1 mL in 1 VIAL. TYPE 0

Vial and contents must be discarded 30 days after initial use.

Store between 20° to 25°C (68° to 77°F) [See USP Controlled Room Temperature]. Epinephrine is light sensitive. Protect from light and freezing.

Inspect visually for particulate matter and discoloration prior to administration. Do not use the solution if it is colored or cloudy, or if it contains particulate matter.

Repackaged and Distributed By:

Remedy Repack, Inc.

625 Kolter Dr. Suite #4 Indiana, PA 1-724-465-8762

17 PATIENT COUNSELING INFORMATION

Advise patients or their caregivers about common adverse reactions associated with the use of epinephrine including an increase in heart rate, the sensation of a more forceful heartbeat, palpitations, sweating, nausea and vomiting, difficulty breathing, pallor, dizziness, weakness or shakiness, headache, apprehension, nervousness, or anxiety. These symptoms and signs usually subside rapidly, especially with rest, quiet and recumbent positioning.

Warn patients with a good response to initial treatment about the possibility of recurrence of symptoms and instruct patients to obtain proper medical attention if symptoms return.

Warn patients with diabetes that they may develop increased blood glucose levels following epinephrine administration.

Rare cases of serious skin and soft tissue infections, including necrotizing fasciitis and myonecrosis caused by Clostridia (gas gangrene), have been reported at the injection site following epinephrine injection for anaphylaxis. Advise patients to seek medical care if they develop signs or symptoms of infection, such as persistent redness, warmth, swelling, or tenderness, at the epinephrine injection site [see Warnings and Precautions (5.2)] .

Repackaged By / Distributed By: RemedyRepack Inc.

625 Kolter Drive, Indiana, PA 15701

(724) 465-8762

PRINCIPAL DISPLAY PANEL

DRUG: Adrenalin

GENERIC: epinephrine

DOSAGE: INJECTION

ADMINSTRATION: INTRAMUSCULAR

NDC: 70518-1342-0

NDC: 70518-1342-1

PACKAGING: 1 mL in 1 VIAL

OUTER PACKAGING: 25 in 1 CARTON

ACTIVE INGREDIENT(S):

- EPINEPHRINE 1mg in 1mL

INACTIVE INGREDIENT(S):

- SODIUM CHLORIDE
- SODIUM METABISULFITE
- SODIUM HYDROXIDE
- TARTARIC ACID
- EDETATE DISODIUM
- HYDROCHLORIC ACID
- WATER